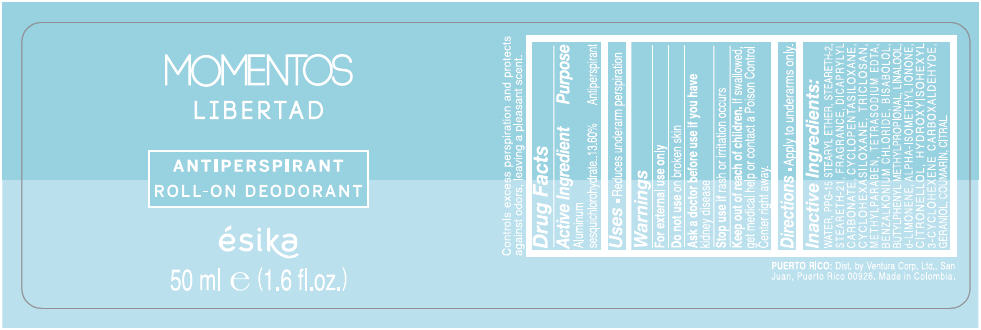 DRUG LABEL: ESIKA MOMENTOS LIBERTAD ANTIPERSPIRANT ROLL-ON DEODORANT
NDC: 14141-844 | Form: EMULSION
Manufacturer: Bel Star S.A. (Colombia)
Category: otc | Type: HUMAN OTC DRUG LABEL
Date: 20191116

ACTIVE INGREDIENTS: ALUMINUM SESQUICHLOROHYDRATE 0.136 g/1 mL
INACTIVE INGREDIENTS: WATER; PPG-15 STEARYL ETHER; STEARETH-2; STEARETH-21; DICAPRYLYL CARBONATE; CYCLOMETHICONE 5; CYCLOMETHICONE 6; TRICLOSAN; METHYLPARABEN; EDETATE SODIUM; BENZALKONIUM CHLORIDE; LEVOMENOL; BUTYLPHENYL METHYLPROPIONAL; LINALOOL, (+/-)-; LIMONENE, (+)-; ISOMETHYL-.ALPHA.-IONONE; .BETA.-CITRONELLOL, (R)-; HYDROXYISOHEXYL 3-CYCLOHEXENE CARBOXALDEHYDE; GERANIOL; COUMARIN; CITRAL

ESIKA MOMENTOS LIBERTAD ANTIPERSPIRANT ROLL-ON DEODORANT

Drug Facts

Active Ingredient

ALUMINUM SESQUICHLOROHYDRATE

Purpose

13.60 % Antiperspirant

Uses

- Reduces underarm perspiration

Warnings

For external use only

Do not use on broken skin

Ask a doctor before use if you have kidney disease

Stop use if rash or irritation occurs

Keep out of reach of children.If swallowed, get medical help or contact a Poison Control Center right away.

Directions

- Apply to underarms only.

Inactive ingredients

WATER, PPG-15 STEARYL ETHER, STEARETH-2, STEARETH-21, FRAGRANCE, DICAPRYLYL CARBONATE, CYCLOPENTASILOXANE, CYCLOHEXASILOXANE, TRICLOSAN, METHYLPARABEN, TETRASODIUM EDTA, BENZALKONIUM CHLORIDE, BISABOLOL, BUTYLPHENYL METHYLPROPIONAL, LINALOOL, d-LIMONENE, ALPHA-ISOMETHYL IONONE, CITRONELLOL, HYDROXYISOHEXYL 3-CYCLOHEXENE CARBOXALDEHYDE, GERANIOL, COUMARIN, CITRAL.

Dist. by Ventura Corp, Ltd., San
Juan, Puerto Rico 00926.

PRINCIPAL DISPLAY PANEL - 50 ml Bottle Label

MOMENTOS
LIBERTAD

ANTIPERSPIRANT
ROLL-ON DEODORANT

ésika
50 ml e (1.6 fl.oz.)